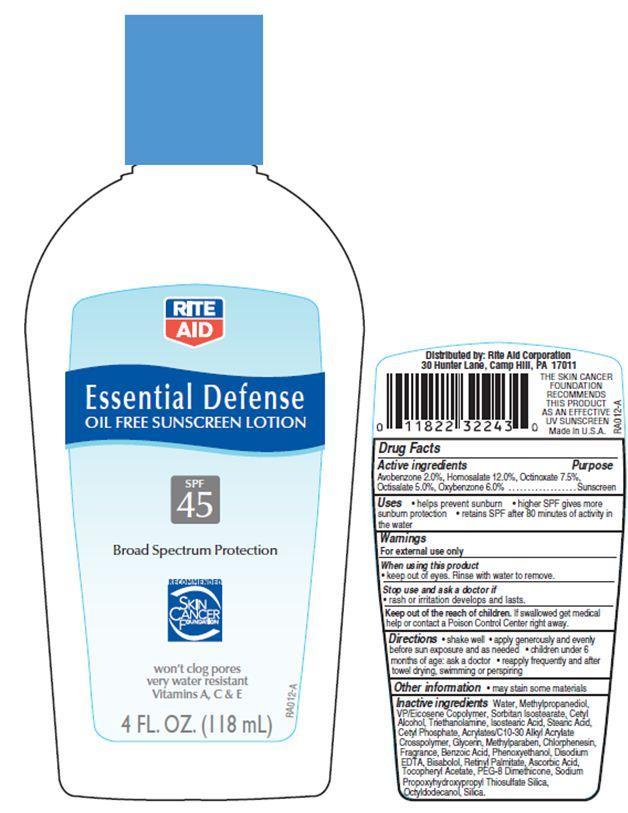 DRUG LABEL: Rite Aid Essential Defense
NDC: 11822-9004 | Form: LOTION
Manufacturer: RITE AID CORPORATION
Category: otc | Type: HUMAN OTC DRUG LABEL
Date: 20121121

ACTIVE INGREDIENTS: AVOBENZONE 2 g/100 g; HOMOSALATE 12 g/100 g; OCTISALATE 5 g/100 g; OCTINOXATE 7.5 g/100 g; OXYBENZONE 6 g/100 g
INACTIVE INGREDIENTS: WATER; METHYLPROPANEDIOL ; CETYL ALCOHOL; TROLAMINE; ISOSTEARIC ACID; STEARIC ACID; SORBITAN ISOSTEARATE; CETYL PHOSPHATE; GLYCERIN; METHYLPARABEN; PROPYLPARABEN; .ALPHA.-TOCOPHEROL ACETATE; EDETATE DISODIUM; CHLORPHENESIN; BENZOIC ACID; PHENOXYETHANOL; LEVOMENOL; VITAMIN A PALMITATE; ASCORBIC ACID; PEG-8 DIMETHICONE; OCTYLDODECANOL; SILICON DIOXIDE

Drug Facts

Active Ingredients

Avobenzone 2.0 %

Homosalate 12.0%

Octinoxate 7.5%

Octisalate 5.0%

Oxybenzone 6.0%

Purpose

Sunscreen

Uses

- helps prevent sunburn
- higher SPF gives more sunburn protection
- retains SPF after 80 minutes of activity in the water

Warnings

For external use only

When using this product

- keep out of eyes. Rinse with water to remove.

stop use and ask a doctor if

- rash or irritation develops and lasts

Keep out of reach of children.

If swallowed get medical help or contact a Poison Control Center right away.

Other Information

- may stain some materials

Directions

- shake well
- apply generously before sun exposure and as needed
- children under 6 months of age:ask a doctor
- reapply frequently and after towel drying, swimming or perspiring.

Inactive Ingredients

Water, Methylpropanediol, VP/Eicosene Copolymer, Sorbitan Isostearate, Cetyl Alcohol, Triethanolamine, Isostearic Acid, Stearic Acid, Cetyl Phosphate, Acrylates/C10-30 Alkyl Acrylate Crosspolymer, Glycerin, Methylparaben, Chlorphenesin, Fragrance, Benzoic Acid, Phenoxyethanol, Disodium EDTA, Bisabolol, Retinyl Palmitate, Ascorbic Acid, Tocopheryl Acetate, PEG-8 Dimethicone, Sodium Propoxyhydroxypropyl Thiosulfate Silica, Octyldodecanol, Silica.

Principal Display Panel

RITE
AID
Essential Defence
OIL FREE SUNSCREEN LOTION
SPF
45
Broad Spectrum Protection
RECOMMENDED
SKIN CANCER
FOUNDATION
won't clog pores
very water resistance
Vitamins A, C and E
4 FL. OZ. (118 mL)